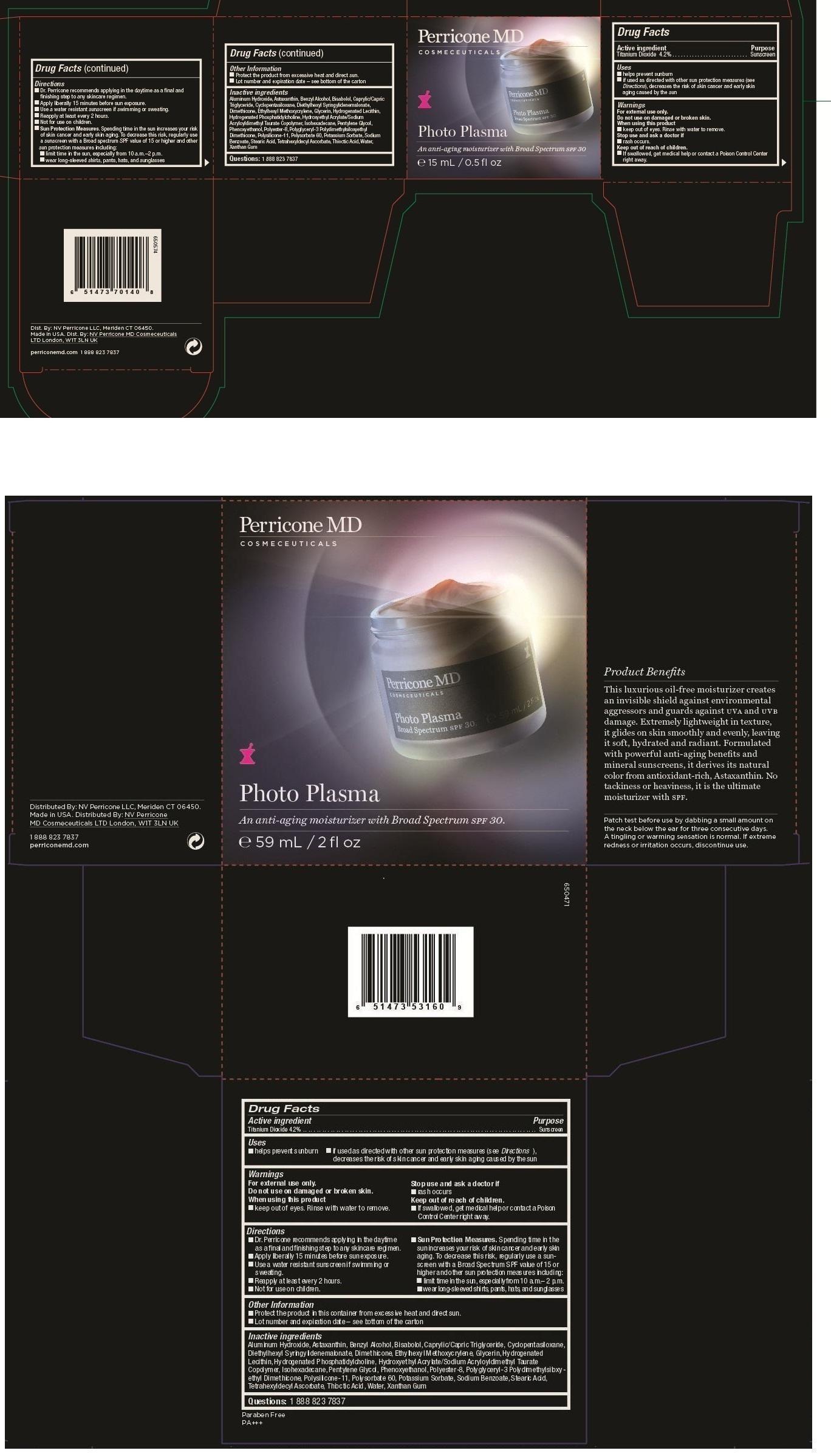 DRUG LABEL: Photo Plasma
NDC: 61383-201 | Form: Cream
Manufacturer: Dimensional Merchandising Inc.
Category: otc | Type: HUMAN OTC DRUG LABEL
Date: 20140306

ACTIVE INGREDIENTS: TITANIUM DIOXIDE 4.2 g/100 mL
INACTIVE INGREDIENTS: ALUMINUM HYDROXIDE; ASTAXANTHIN; BENZYL ALCOHOL; LEVOMENOL; MEDIUM-CHAIN TRIGLYCERIDES; CYCLOMETHICONE 5; DIETHYLHEXYL SYRINGYLIDENEMALONATE; DIMETHICONE; ETHYLHEXYL METHOXYCRYLENE; GLYCERIN; HYDROGENATED SOYBEAN LECITHIN; HYDROXYETHYL ACRYLATE/SODIUM ACRYLOYLDIMETHYL TAURATE COPOLYMER (45000 MPA.S AT 1%); ISOHEXADECANE; PENTYLENE GLYCOL; PHENOXYETHANOL; POLYESTER-8 (1400 MW, CYANODIPHENYLPROPENOYL CAPPED); POLYGLYCERYL-3 LAURATE; POLYSILICONE-15; POLYSORBATE 60; POTASSIUM SORBATE; SODIUM BENZOATE; STEARIC ACID; TETRAHEXYLDECYL ASCORBATE; .ALPHA.-LIPOIC ACID; WATER; XANTHAN GUM

Photo Plasma

Active ingredient

Titanium dioxide 4.2%

Purpose

Sunscreen

Keep out of reach of children

If swallowed, get medical help or contact a Posion Control Center right away.

Uses

- Helps prevents sun burn
- If used as directed with other sun protection measures (see Directions) decreases the risk of skin cancer and early skin aging caused by the sun

Warnings

For extenal use only

Do not use on damaged or broken skin

When using this product

- keep out of eyes, Rinse with water to remove.

Stop use and ask a doctor if

- rash occurs.

Directions

- Dr.Perricone recommends applying in the day time as a final and finishing step to any skin care regimen.
- Apply liberally 15 minutes before sun exposure.
- Use a water resistant sunscreen if swimming or sweating.
- Reapply at least every 2 hours.
- Not for use on Children.
- Sun Protection measures-Spending time in the sun increases your risk of skin cancer and early skin aging. To decrease this risk, regularly use a sun screen with a Broad Spectrum SPF of 15 or higher and other sun protection measures including
- limit time in the sun especially from 10 am. - 2 pm.
- wear long sleaved shirts, Pants, hats and sun glasses

Other Information

- Protect the product from excessive heat and direct sun.
- Lot number and expiration date -see bottom of the carton

Inactive Ingredients

Aluminum Hydroxide, Astaxanthin, Benzyl alcohol, Bisabolol,Caprylic /Capric Triglyceride, Cyclopentasiloxane, Diethylhexyl Syringy lidenemalonate, Dimethicone, Ethylhexyl Methoxycrylene, Glycerin, Hydrogenated Lecithin, Hydrogenated phosphatidylcholine, Hydroxyethyl Acrylate /Sodium Acrylodimethyl Taurate copolymer, Isohexadecane, Pentylene Glycol, Phenoxyethanol, Polyester-8 ,Polyglyceryl-3 Polydimethylsibxy-ethyl Dimethicone,Polysilicone-11,Polysorbate 60, Potassium Sorbate, Sodium Benzoate, Stearic Acid, Tetrahexyldecyl Ascorbate, Thioctic Acid, Water, Xanthan Gum.

Questions:1 888 823 7837

Distributed by:NV Perricone LLC, Meriden CT 06 450,

Made in USA

Distributed by:NV Perricone MD Cosmeceuticals LTD London, WIT 3LN UK